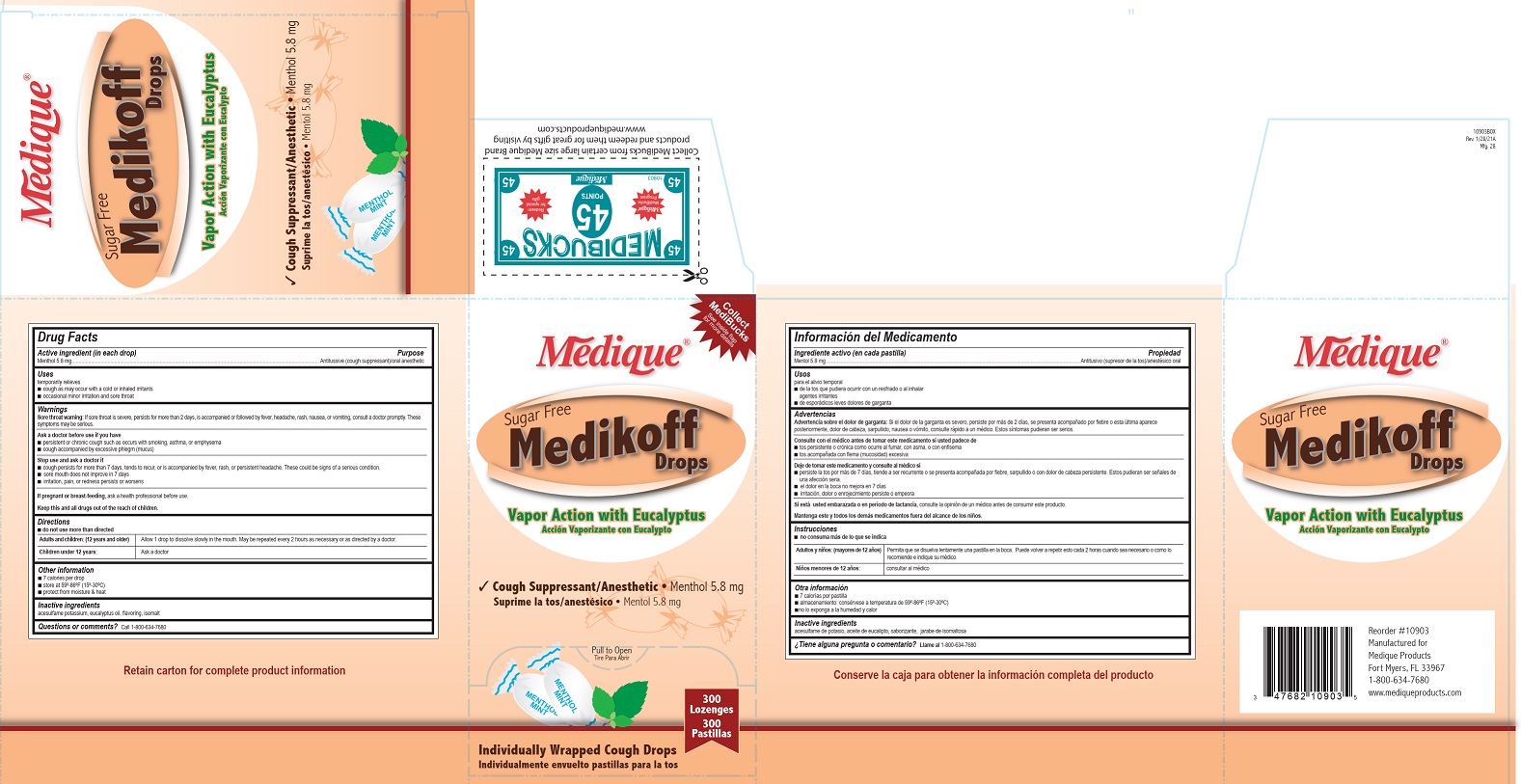 DRUG LABEL: Medique Sugar Free Medikoff Drops
NDC: 47682-110 | Form: LOZENGE
Manufacturer: Unifirst First Aid Corporation
Category: otc | Type: HUMAN OTC DRUG LABEL
Date: 20250908

ACTIVE INGREDIENTS: MENTHOL 5.8 mg/1 1
INACTIVE INGREDIENTS: ACESULFAME POTASSIUM; EUCALYPTUS OIL; ISOMALT

MEDIQUE SUGAR FREE MEDIKOFF DROPS

Drug Facts

Active ingredient (in each drop)

Menthol 5.8 mg

Purpose

Antitussive (cough suppressant)/oral anesthetic

Uses

temporarily relieves

■ cough as may occur with a cold or inhaled irritants

■ occasional minor irritation and sore throat

Warnings

Sore throat warning: If sore throat is severe, persists for more than 2 days, is accompanied or followed by fever, headache, rash, nausea, or vomiting, consult a doctor promptly. These symptoms may be serious.

Ask a doctor before use if you have

- persistent or chronic cough such as occurs with smoking, asthma, or emphysema
- cough accompanied by excessive phlegm (mucus)

Stop use and ask a doctor if

- cough persists for more than 7 days, tends to recur, or is accompanied by fever, rash, or persistent headache. These could be signs of a serious condition.
- sore mouth does not improve in 7 days
- irritation, pain, or redness persists or worsens

PREGNANCY OR BREAST FEEDING

If pregnant or breast-feeding, ask a health professional before use.

KEEP OUT OF REACH OF CHILDREN

Keep this and all drugs out of the reach of children.

Directions

- do not use more than directed

Adults and Children (12 years and older)

Allow 1 drop to dissolve slowly in the mouth. May be repeated every 2 hours as necessary or as directed by a doctor.

Children under 12 years: Ask a doctor

Other information

- 7 calories per drop
- store at 59º-86ºF (15º-30ºC)
- protect from moisture & heat

Inactive ingredients

acesulfame potassium, eucalyptus oil, flavoring, isomalt

Questions or comments? 1-800-634-7680

Medique Medikoff Sugar Free

Medique ®

Sugar Free Medikoff Drops

Vapor Action with Eucalyptus

Accion Vaporizante con Eucalypto

Cough Supressant/Anesthetic • Menthol 5.8mg

Suprima la tos/anestesico • Mentol 5.8 mg

Pull to Open

Tire Para Abrir

300 Lozenges

300 Pastillas

Individually Wrapped Cough Drops

Individualmento envuelto pastillas para la tos

Collect MediBucks

See inside flap for more details